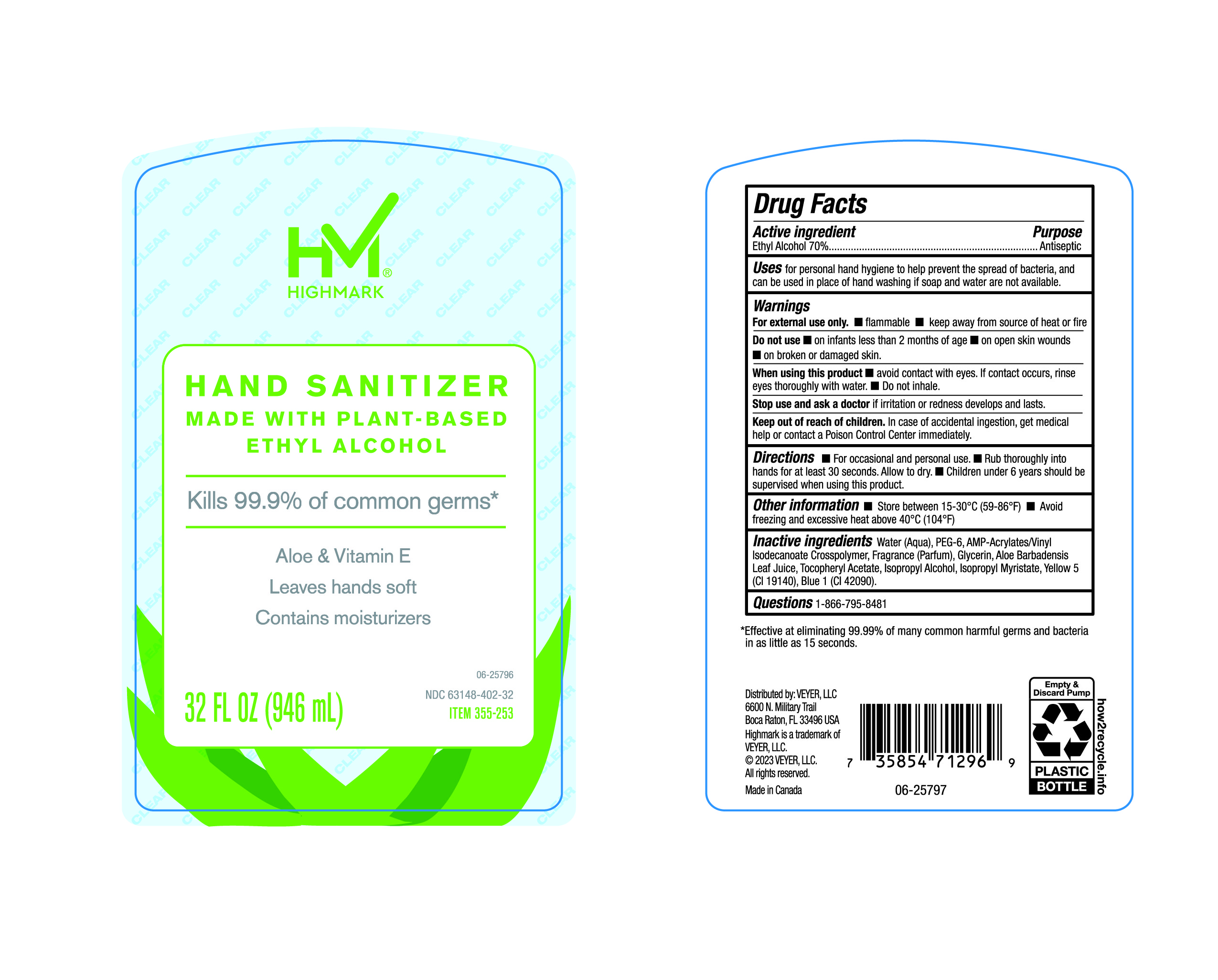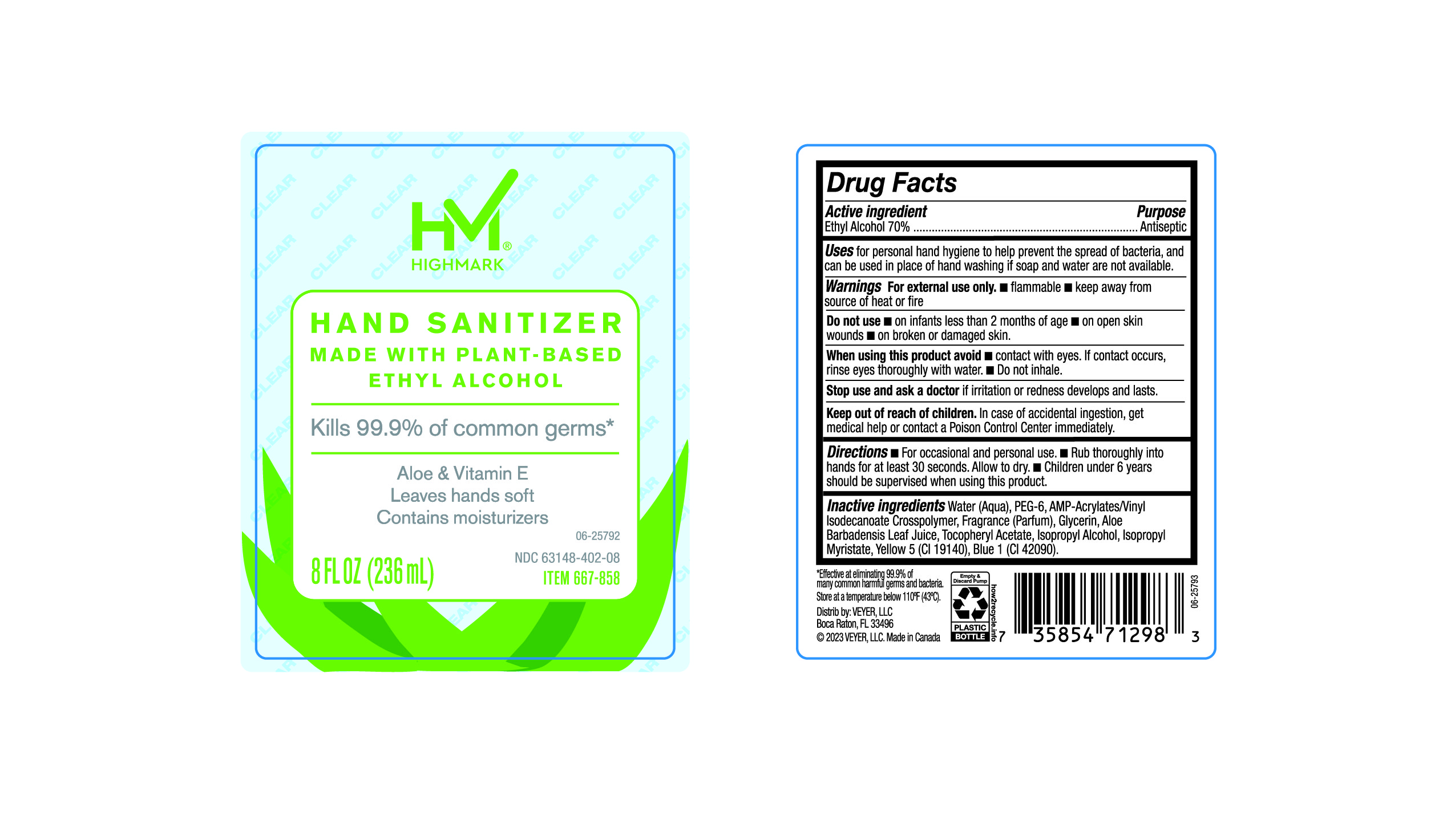 DRUG LABEL: HiGHMARK
NDC: 63148-402 | Form: LIQUID
Manufacturer: Apollo Health and Beauty Care
Category: otc | Type: HUMAN OTC DRUG LABEL
Date: 20241020

ACTIVE INGREDIENTS: ALCOHOL 70 mL/100 mL
INACTIVE INGREDIENTS: WATER; FRAGRANCE CLEAN ORC0600327; ACRYLATES/VINYL ISODECANOATE CROSSPOLYMER (10000 MPA.S NEUTRALIZED AT 0.5%); ALOE VERA LEAF; ISOPROPYL MYRISTATE; BASIC BLUE 1; GLYCERIN; ALPHA-TOCOPHEROL ACETATE; ISOPROPYL ALCOHOL; BASIC YELLOW 5; POLYETHYLENE GLYCOL 300

63148-402-03, 63148-402- HIMARK

ACTIVE INGREDIENT

Ethyl Alcohol 70%

PURPOSE

Antiseptic

Uses

For personal hand hygine to help prevent the spread of bacteria, and can be used in place of hand washing if soap and water are not available.

Warnings

For external use only.

- Flammable
- Keep away from source of heat or fire.

Do not use

- On infants less than 2 months of age.
- On open skin wounds
- On broken or damaged skin.

When using this product avoid

- Contact with eyes. If contact occurs, rinse eyes throughly with water.
- Do not inhale.

Stop use and ask a doctor

If irritation or redness develop and lasts.

Keep out of reach of children

In case of accidental ingestion, get medical help or contact a Poison Control Center immediately.

Directions

- For occasional and personal use.
- Rub thoroughly into hands for at least 30 seconds. Allow to dry.
- Children under 6 years should be supervised when using this product.

Inactive Ingredients

Water (Aqua), PEG-6, AMP-Acrylates/Vinyl Isodecanoate Crosspolymer, Fragrance (Parfum), Glycerin, Aloe Barbadensis Leaf Juice, Tocopheryl Acetate, Isopropyl Alcohol, Isopropyl Myristate, Yellow 5 (Cl 19140), Blue 1 (Cl 42090).

Questions

1-866-795-8481